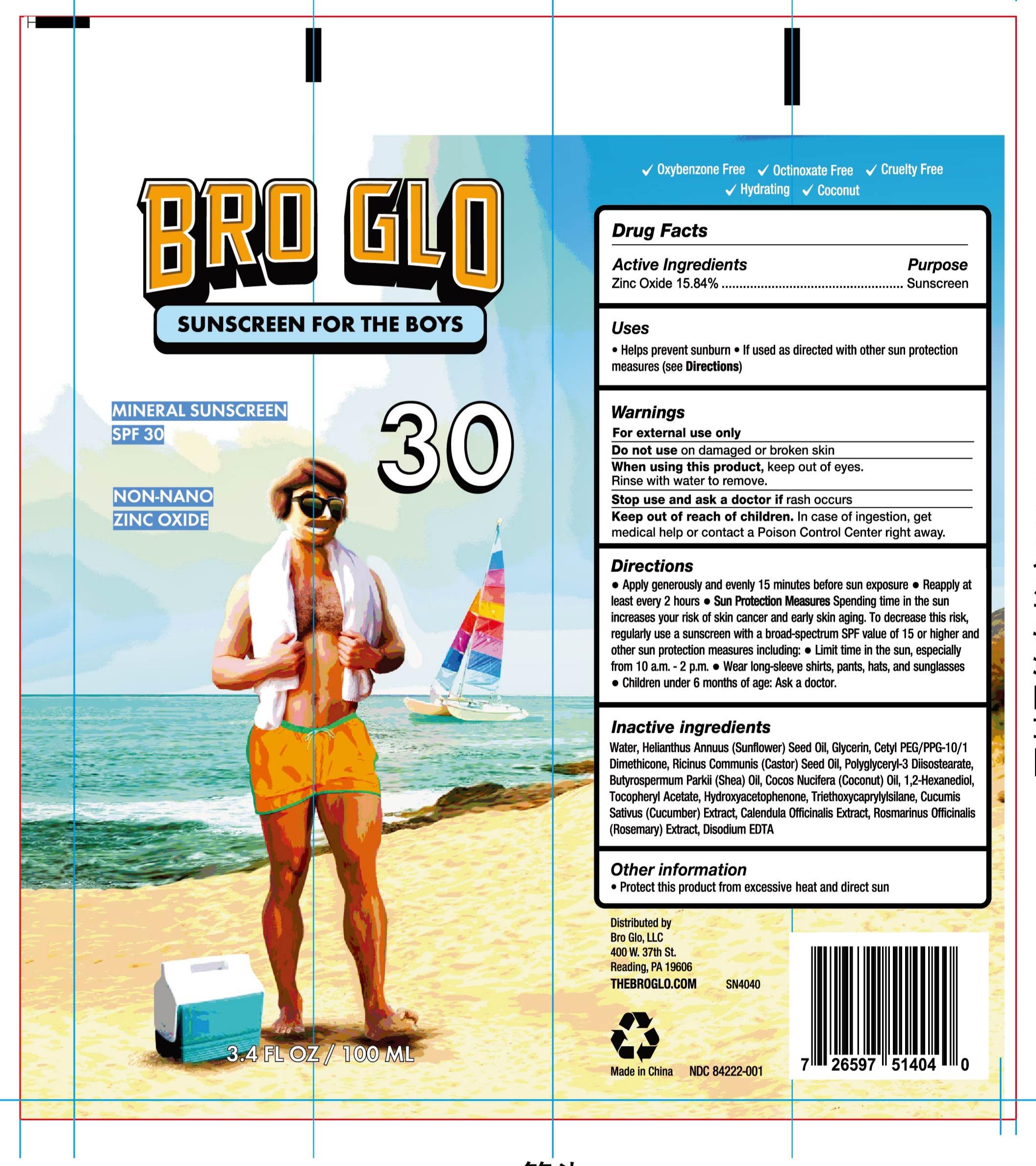 DRUG LABEL: BRO GLO Sunscreen for the boys SPF30
NDC: 84222-001 | Form: LOTION
Manufacturer: Foshan Miwei Cosmetics Co., Ltd.
Category: otc | Type: HUMAN OTC DRUG LABEL
Date: 20251019

ACTIVE INGREDIENTS: ZINC OXIDE 16 g/100 mL
INACTIVE INGREDIENTS: CETYL PEG/PPG-10/1 DIMETHICONE (HLB 2) 3 mL/100 mL; POLYGLYCERYL-3 DIISOSTEARATE 2.5 mL/100 mL; EDETATE DISODIUM 0.05 mL/100 mL; BUTYROSPERMUM PARKII (SHEA) OIL 3 mL/100 mL; HYDROXYACETOPHENONE 0.5 mL/100 mL; CALENDULA OFFICINALIS FLOWER 0.01 mL/100 mL; COCOS NUCIFERA (COCONUT) OIL 8 mL/100 mL; CASTOR OIL 0.5 mL/100 mL; 1,2-HEXANEDIOL 0.5 mL/100 mL; .ALPHA.-TOCOPHEROL ACETATE 0.5 mL/100 mL; CUCUMBER 0.01 mL/100 mL; ROSEMARY 0.01 mL/100 mL; GLYCERIN 10 mL/100 mL; WATER 49 mL/100 mL; HELIANTHUS ANNUUS (SUNFLOWER) SEED OIL 8 mL/100 mL

SN4040 BRO GLO Sunscreen for the boys SPF30

PURPOSE

Sunscreen

ACTIVE INGREDIENT

Zinc Oxide(Non-nano) 16%

When using this product, keep out of eyes

Rinse with water to remove

WARNINGS

For external use only
Do not use on damaged or broken skin
When using this product, keep out of eyes.
Rinse with water to remove.
Stop use and ask a doctor if rash occurs
Keep out of reach of children. In case of ingestion, get
medical help or contact a Poison Control Center right away.

Do not use on damaged or broken skin

INDICATIONS AND USAGE

*Help prevent sunburn

*If used as directed with other sun protection measures(see Directions)

STOP USE

Stop using and ask a doctor if a rash occurs

Keep out of reach of children. In case of ingestion, get medical help or contact a Poison Control Center right away.

DOSAGE AND ADMINISTRATION

*Apply generously and evenly 15 minutes before sun exposure

*Reapply at least every 2 hours

Sun Protection Measures: Spending time in the sun increases your risk of skin cancer and early skin aging. To decrease this risk, regularly use sunscreen with a broad spectrum SPF value of 15 or higher and other sun protection measures including:

*Limit time in the sun, especially from 10 am.-2 pm.

*Wear long-sleeve shirts, pants, hats, and sunglasses Children under 6 months of age : Ask a doctor

OTHER SAFETY INFORMATION

Protect this product from excessive heat and direct sun

INACTIVE INGREDIENT

Water, Glycerin, Helianthus Annuus (Sunflower) Seed Oil, Cocos Nucifera (Coconut) Oil, Cetyl PEG/PPG-10/1 Dimethicone, Butyrospermum Parkii (Shea) Oil, Polyglyceryl-3 Diisostearate, Ricinus Communis (Castor) Seed Oil, Hydroxyacetophenone, Tocopheryl Acetate, 1,2-Hexanediol, Triethoxycaprylylsilane, Disodium EDTA, Cucumis Sativus (Cucumber) Extract, Calendula Officinalis Extract, Rosmarinus Officinalis (Rosemary) Extract

RECENT MAJOR CHANGES

INDICATIONS & USAGE SECTION

Update to more accurate warning description

DOSAGE & ADMINISTRATION SECTION

Update to more accurate Direction description